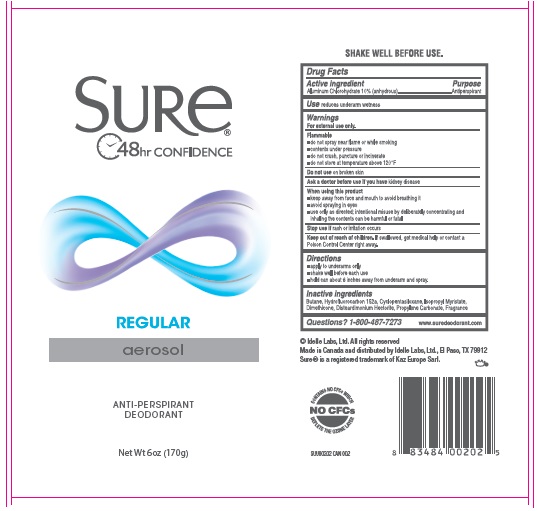 DRUG LABEL: Sure Antiperspirant Deodorant Regular
NDC: 41595-5518 | Form: AEROSOL
Manufacturer: Idelle Labs, Ltd
Category: otc | Type: HUMAN OTC DRUG LABEL
Date: 20230102

ACTIVE INGREDIENTS: ALUMINUM CHLOROHYDRATE 10 g/100 g
INACTIVE INGREDIENTS: BUTANE; 1,1-DIFLUOROETHANE; CYCLOMETHICONE 5; ISOPROPYL MYRISTATE; DIMETHICONE; DISTEARDIMONIUM HECTORITE; PROPYLENE CARBONATE

SURE ANTIPERSPIRANT DEODORANT REGULAR

Active ingredient

Aluminum Chlorohydrate 10% (anhydrous)

Purpose

Antiperspirant

Use

Reduces underarm wetness

Warnings

For external use only.

Flammable

- do not spray near flame or while smoking
- contents under pressure
- do not crush, puncture or incinerate
- do not store at temperature above 120°F

Do not use

On broken skin

Ask a doctor before use

if you have kidney disease

When using this product

- keep away from face and mouth to avoid breathing it
- avoid spraying in eyes
- use only as directed; intentional misuse by deliberately concentrating and inhaling the contents can be harmful or fatal

Stop use

if rash or irritation occurs

Keep out of reach of children.

If swallowed, get medical help or contact a Poison Control Center right away.

Directions

- apply to underarms only
- shake well before each use
- hold can about 6 inches away from underarm and spray.

Inactive ingredients

Butane, Hydrofluorocarbon 152a, Cyclopentasiloxane, Isopropyl Myristate, Dimethicone, Disteardimonium Hectorite, Propylene Carbonate, Fragrance

Questions?

1-800-487-7273 www.suredeodorant.com

SURE®

REGULAR

aerosol

ANTI-PERSPIRANT

DEODORANT

Net Wt 6 oz (170g)

© Idelle Labs, Ltd. All rights reserved

Made in Canada and distributed by Idelle Labs, Ltd., El Paso, TX 79912

Sure® is a registered trademark of Kaz EUROPE Sarl.